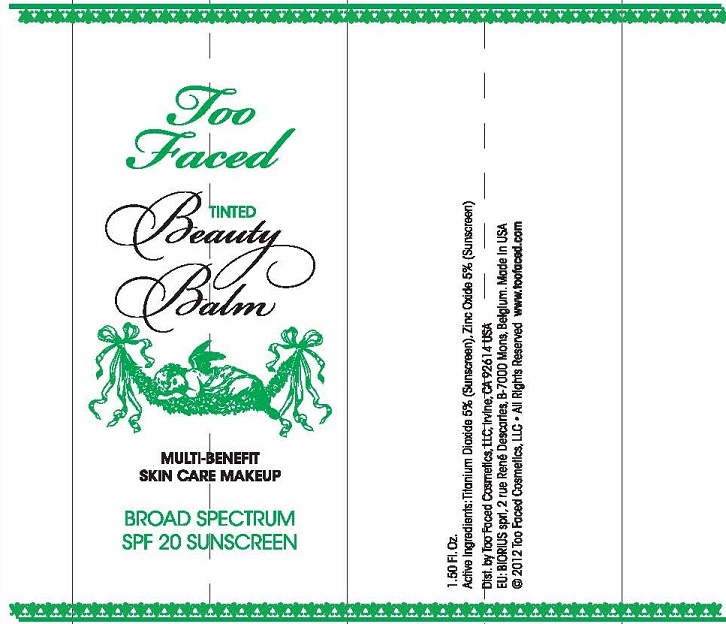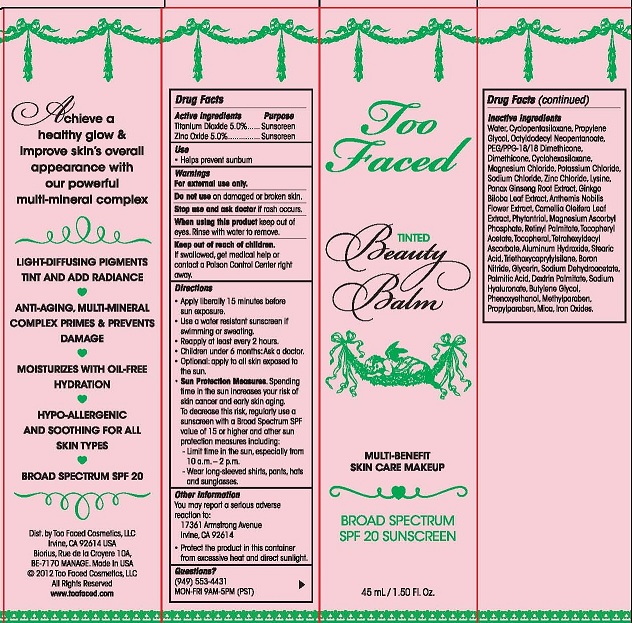 DRUG LABEL: Too Faced Tinted Beauty Balm
NDC: 79596-090 | Form: CREAM
Manufacturer: TOO FACED COSMETICS
Category: otc | Type: HUMAN OTC DRUG LABEL
Date: 20130108

ACTIVE INGREDIENTS: TITANIUM DIOXIDE 5 g/100 mL; ZINC OXIDE 5 g/100 mL
INACTIVE INGREDIENTS: WATER; CYCLOMETHICONE 5; PROPYLENE GLYCOL; OCTYLDODECYL NEOPENTANOATE; PEG/PPG-18/18 DIMETHICONE; DIMETHICONE; CYCLOMETHICONE 6; MAGNESIUM CHLORIDE; POTASSIUM CHLORIDE; SODIUM CHLORIDE; ZINC CHLORIDE; LYSINE; PANAX GINSENG ROOT WATER; GINKGO BILOBA WHOLE; CHAMAEMELUM NOBILE FLOWER; CAMELLIA OLEIFERA LEAF; PHYTANTRIOL; MAGNESIUM ASCORBYL PHOSPHATE; VITAMIN A PALMITATE; .ALPHA.-TOCOPHEROL ACETATE; TOCOPHEROL; TETRAHEXYLDECYL ASCORBATE; ALUMINUM HYDROXIDE; STEARIC ACID; TRIETHOXYCAPRYLYLSILANE; BORON NITRIDE; GLYCERIN; SODIUM DEHYDROACETATE; PALMITIC ACID; ICODEXTRIN; HYALURONATE SODIUM; BUTYLENE GLYCOL; PHENOXYETHANOL; METHYLPARABEN; PROPYLPARABEN; MICA; BROWN IRON OXIDE

ACTIVE INGREDIENTS

TITANIUM DIOXIDE 5.0%

ZINC OXIDE 5.0%

PURPOSE

SUNSCREEN

USE

- HELPS PREVENT SUNBURN

WARNINGS

FOR EXTERNAL USE ONLY

DO NOT USE ON DAMAGED OR BROKEN SKIN.

STOP USE AND ASK DOCTOR IF RASH OCCURS.

WHEN USING THIS PRODUCT KEEP OUT OF EYES. RINSE WITH WATER TO REMOVE.

KEEP OUT OF REACH OF CHILDREN. IF SWALLOWED, GET MEDICAL HELP OR CONTACT A POISON CONTROL CENTER RIGHT AWAY.

DIRECTIONS

- APPLY LIBERALLY AND SMOOTHLY 15 MINUTES BEFORE SUN EXPOSURE.
- USE A WATER RESISTANT SUNSCREEN IF SWIMMING OR SWEATING.
- REAPPLY AT LEAST EVERY 2 HOURS.
- CHILDREN UNDER 6 MONTHS: ASK A DOCTOR.
- OPTIONAL: APPLY TO ALL SKIN EXPOSED TO THE SUN.
- SUN PROTECTION MEASURES. SPENDING TIME IN THE SUN INCREASES YOUR RISK OF SKIN CANCER AND EARLY SKIN AGING. TO DECREASE THIS RISK, REGULARLY USE A SUNSCREEN WITH A BROAD SPECTRUM SPF OF 15 OR HIGHER AND OTHER SUN PROTECTION MEASURES INCLUDING:
- LIMIT TIME IN THE SUN, ESPECIALLY FROM 10 A.M. - 2 P.M.
- WEAR LONG-SLEEVED SHIRTS, PANTS, HATS AND SUNGLASSES.

OTHER INFORMATION

- YOU MAY REPORT A SERIOUS ADVERSE REACTION TO:
  17361 ARMSTRONG AVENUE
  IRVINE, CA 92614
- PROTECT THE PRODUCT IN THIS CONTAINER FROM EXCESSIVE HEAT AND DIRECT SUNLIGHT.

INACTIVE INGREDIENTS

WATER, CYCLOPENTASILOXANE, PROPYLENE GLYCOL, OCTYLDODECYL NEOPENTANOATE, PEG/PPG-18/18 DIMETHICONE, DIMETHICONE, CYCLOHEXASILOXANE, MAGNESIUM CHLORIDE, POTASSIUM CHLORIDE, SODIUM CHLORIDE, ZINC CHLORIDE, LYSINE, PANAX GINSENG ROOT EXTRACT, GINKGO BILOBA LEAF EXTRACT, ANTHEMIS NOBILIS FLOWER EXTRACT, CAMELLIA OLEIFERA LEAF EXTRACT, PHYTANTRIOL, MAGNESIUM ASCORBYL PHOSPHATE, RETINYL PALMITATE, TOCOPHERYL ACETATE, TOCOPHEROL, TETRAHEXYDECYL ASCORBATE, ALUMINUM HYDROXIDE, STEARIC ACID, TRIETHOXYCAPRYLYLSILOXANE, BORON NITRIDE, GLYCERIN, SODIUM DEHYDROACETATE, PALMITIC ACID, DEXTRIN PALMITATE, SODIUM HYALURONATE, BUTYLENE GLYCOL, PHENOXYETHANOL, METHYLPARABEN, PROPYLPARABEN, MICA, IRON OXIDES.

QUESTIONS?

(949) 553-4431

MON-FRI 9AM-5PM (PST)